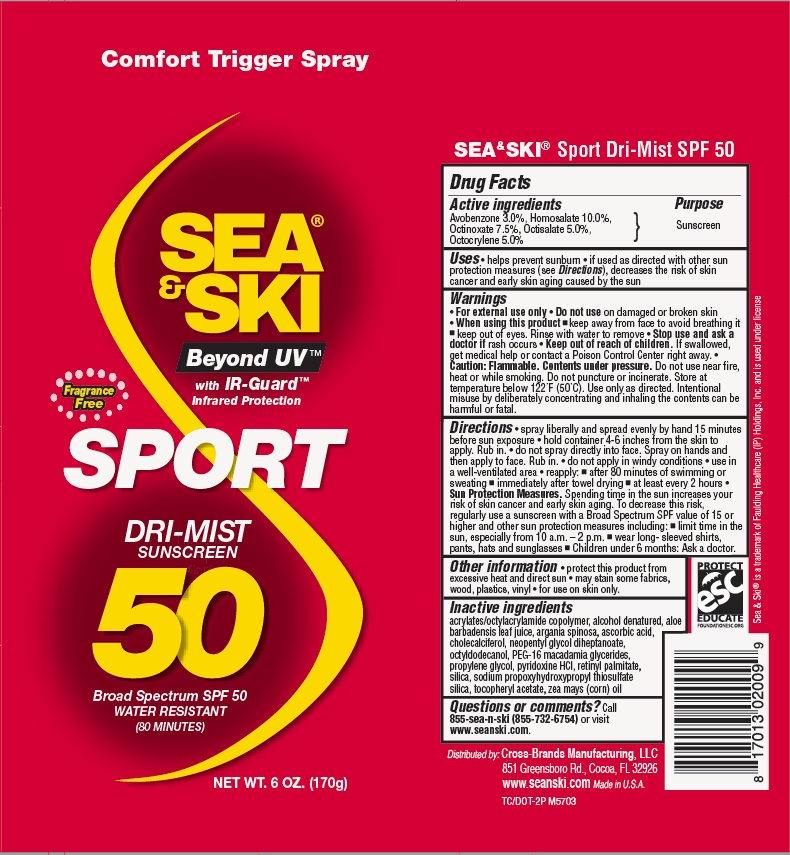 DRUG LABEL: General Protection
NDC: 71153-2009 | Form: AEROSOL, SPRAY
Manufacturer: Cross-Brands Manufacturing LLC
Category: otc | Type: HUMAN OTC DRUG LABEL
Date: 20170104

ACTIVE INGREDIENTS: HOMOSALATE 10 g/1 g; AVOBENZONE 3 g/1 g; OCTINOXATE 7.5 g/1 g; OCTOCRYLENE 5 g/1 g; OCTISALATE 5 g/1 g
INACTIVE INGREDIENTS: ALOE VERA LEAF 0.1 g/1 g

Sea & Ski SPF 50 Sport CSpray